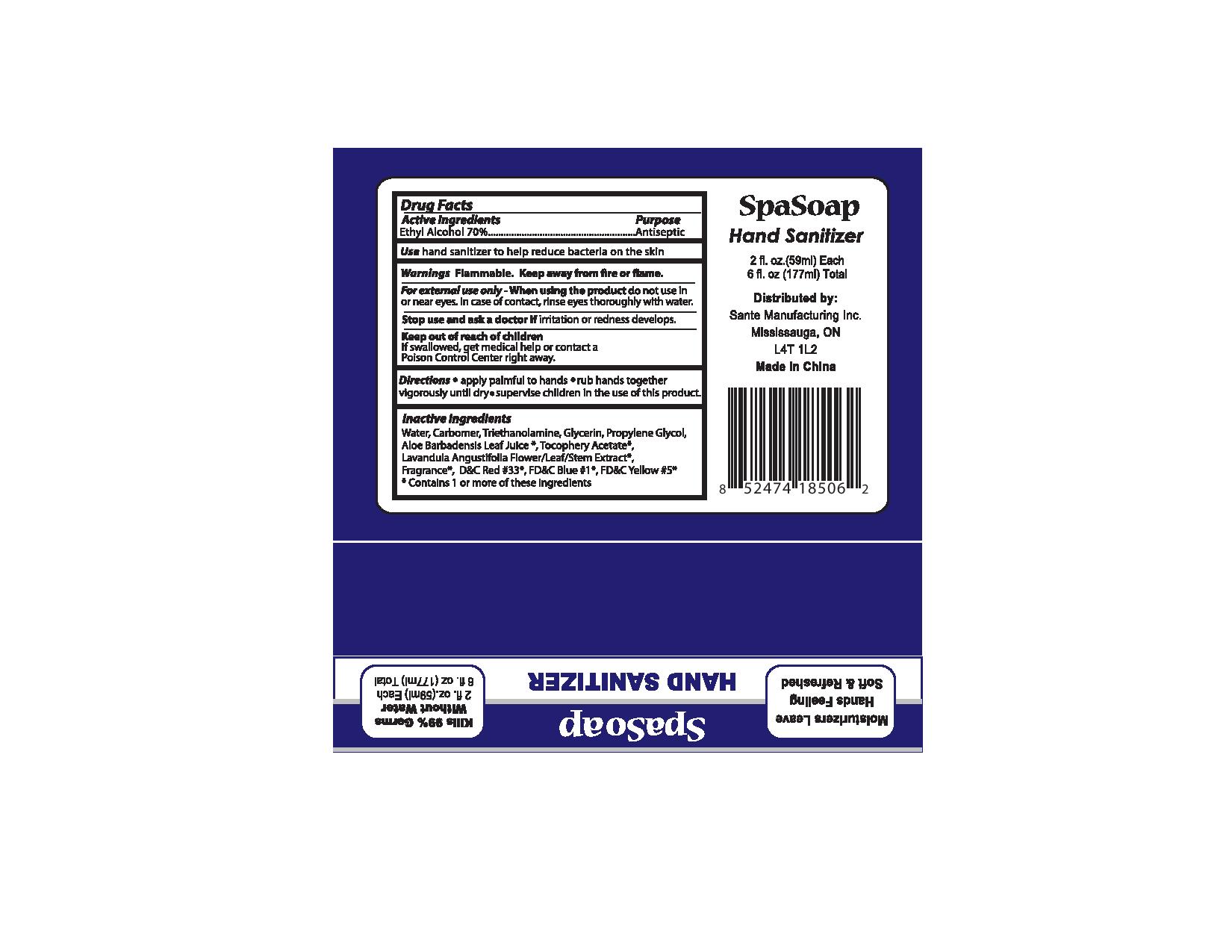 DRUG LABEL: SpaSoap
NDC: 71020-015 | Form: LIQUID
Manufacturer: Sante Manufacturing Inc
Category: otc | Type: HUMAN OTC DRUG LABEL
Date: 20170311

ACTIVE INGREDIENTS: ALCOHOL 700 mL/1000 mL
INACTIVE INGREDIENTS: FD&C YELLOW NO. 5; LAVANDULA ANGUSTIFOLIA WHOLE; WATER; CARBOMER 940; GLYCERIN; ALOE VERA LEAF; .ALPHA.-TOCOPHEROL ACETATE; D&C RED NO. 33; FD&C BLUE NO. 1

Active Ingredients

Ethyl Alcohol 70%

Purpose - Antiseptic

INDICATIONS AND USAGE

Use hand sanitizer to help reduce bacteria on the skin

Warnings

Flammable

OTHER SAFETY INFORMATION

Keep away from fire or flame

For external use only

When using this product do not use in or near eyes. In case of contact, rinse eyes thoroughly with water

Keep out of reach of children

If swallowed, get medical help or contact a Poison Control Center right away

Directions

- apply palmful to hands
  - rub hands together vigorously until dry
  - supervise children in the use of this product

INACTIVE INGREDIENT

Water, Carbomer, Trethanolamine, Glycerin, Propylene Glycol, Alo Barbdensis Leaf Juice*, Tocopherol Acetate*, Lavandula Angustifolia Flower / Leaf / Stem Extract*, Fragrance*, D&C Red # 33*, FD&C Blue # 1*, FD&C Yellow # 5*,

* Contains 1 or more of these ingredients

PACKAGE LABEL

SpaSoap

Hand Sanitizer

2fl.oz (59ml) Each

6 fl.oz (177ml) Total